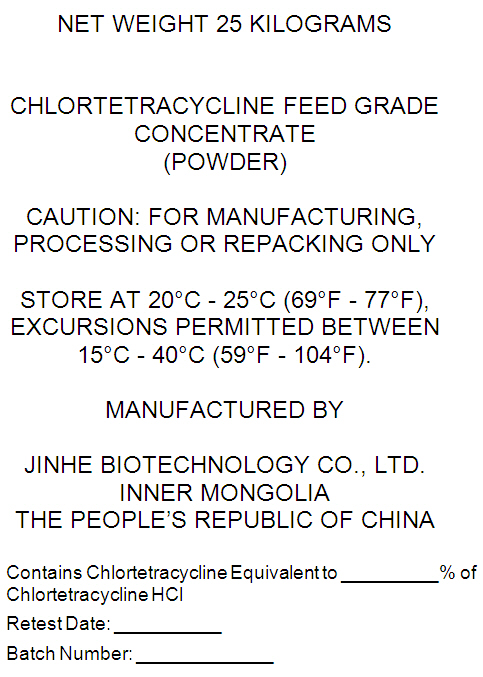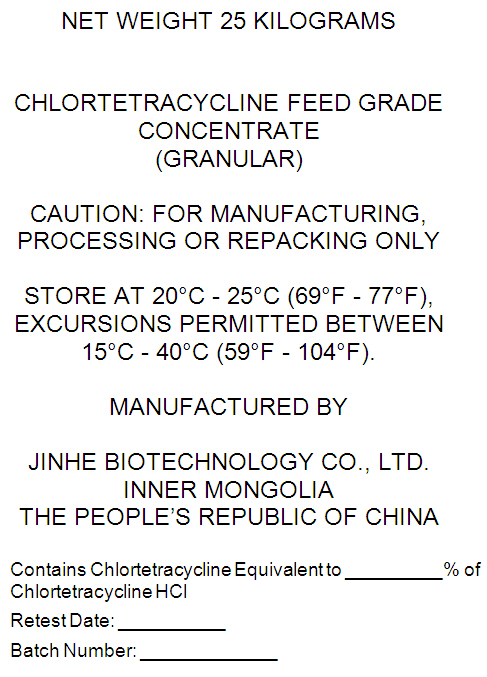 DRUG LABEL: Chlortetracycline Feed Grade
NDC: 66623-001 | Form: POWDER
Manufacturer: Jinhe Biotechnology Co., Ltd.
Category: other | Type: BULK INGREDIENT - ANIMAL DRUG
Date: 20191125

ACTIVE INGREDIENTS: Chlortetracycline Calcium 1 kg/1 kg

CHLORTETRACYCLINE FEED GRADE
CONCENTRATE

PRINCIPAL DISPLAY PANEL - Shipping Label - Powder

NET WEIGHT 25 KILOGRAMS

CHLORTETRACYCLINE FEED GRADE
CONCENTRATE
(POWDER)

CAUTION: FOR MANUFACTURING,
PROCESSING OR REPACKING ONLY

STORE AT 20°C - 25°C (69°F - 77°F),
EXCURSIONS PERMITTED BETWEEN
15°C - 40°C (59°F - 104°F).

MANUFACTURED BY

JINHE BIOTECHNOLOGY CO., LTD.
INNER MONGOLIA
THE PEOPLE'S REPUBLIC OF CHINA

Contains Chlortetracycline Equivalent to % of
Chlortetracycline HCl

Retest Date:

Batch Number:

PRINCIPAL DISPLAY PANEL - Shipping Label - Granular

NET WEIGHT 25 KILOGRAMS

CHLORTETRACYCLINE FEED GRADE
CONCENTRATE
(GRANULAR)

CAUTION: FOR MANUFACTURING,
PROCESSING OR REPACKING ONLY

STORE AT 20°C - 25°C (69°F - 77°F),
EXCURSIONS PERMITTED BETWEEN
15°C - 40°C (59°F - 104°F).

MANUFACTURED BY

JINHE BIOTECHNOLOGY CO., LTD.
INNER MONGOLIA
THE PEOPLE'S REPUBLIC OF CHINA

Contains Chlortetracycline Equivalent to % of
Chlortetracycline HCl

Retest Date:

Batch Number: